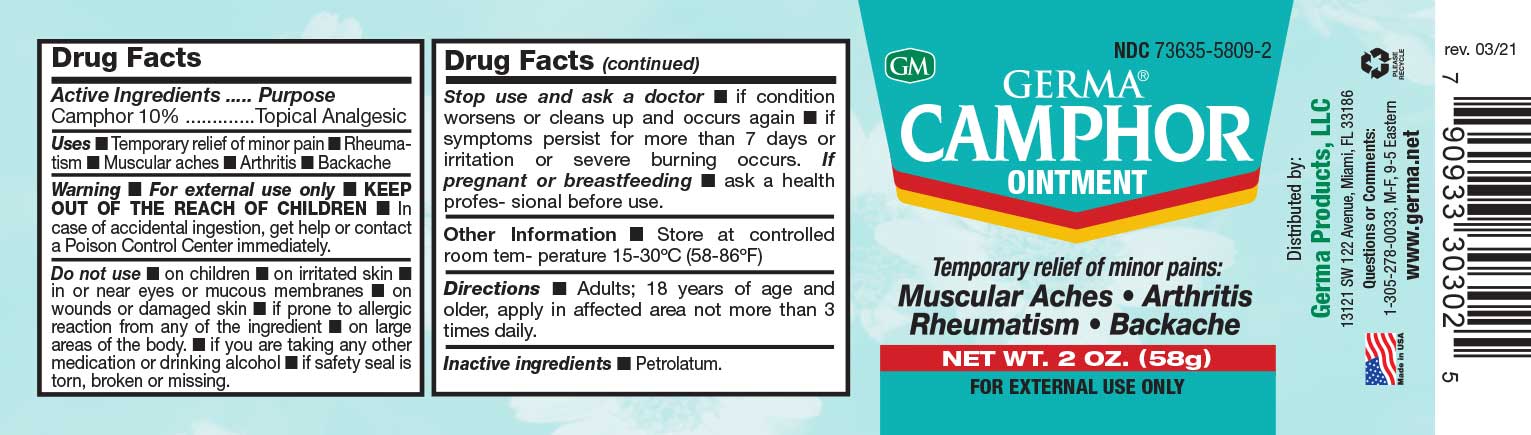 DRUG LABEL: Germa Camphor
NDC: 73635-5809 | Form: OINTMENT
Manufacturer: Germa Products, LLC
Category: otc | Type: HUMAN OTC DRUG LABEL
Date: 20251010

ACTIVE INGREDIENTS: CAMPHOR (SYNTHETIC) 100 mg/1 mL
INACTIVE INGREDIENTS: WHITE PETROLATUM

Camphor Ointment

Active Ingredient

Camphor 10%

Uses

Temporary relief of minor pain • Rheumatism • Muscular aches • Arthritis • Backache

Do not use • on children • on irritated skin • in or near eyes or mucous membranes • on wounds or damaged skin • if prone to allergic reaction from any of the ingredient • on large areas of the body. • if you are taking any other medication or drinking alcohol • if safety seal is torn, broken or missing.

Purpose

Topical Analgesic

Warnings

For external use only

Do not use • on children • on irritated skin • in or near eyes or mucous membranes • on wounds or damaged skin • if prone to allergic reaction from any of the ingredient • on large areas of the body. • if you are taking any other medication or drinking alcohol • if safety seal is torn, broken or missing.

Warnings

KEEP OUT OF THE REACH OF CHILDREN

In case of accidental ingestion, seek professional assistance or contact a Poison Control Center immediately.

PREGNANCY OR BREAST FEEDING

If pregnant or breastfeeding • ask a health professional before use.

Stop use and ask a doctor • if condition worsens or cleans up and occurs again • if symptoms persist for more than 7 days or irritation or severe burning occurs.

Other Information

Store at controlled room temperature 15-30ºC (59-86ºF)

Directions

Adults; 18 years of age and older, apply in affected area not more than 3 times daily.

Inactive Ingredients

Petrolatum